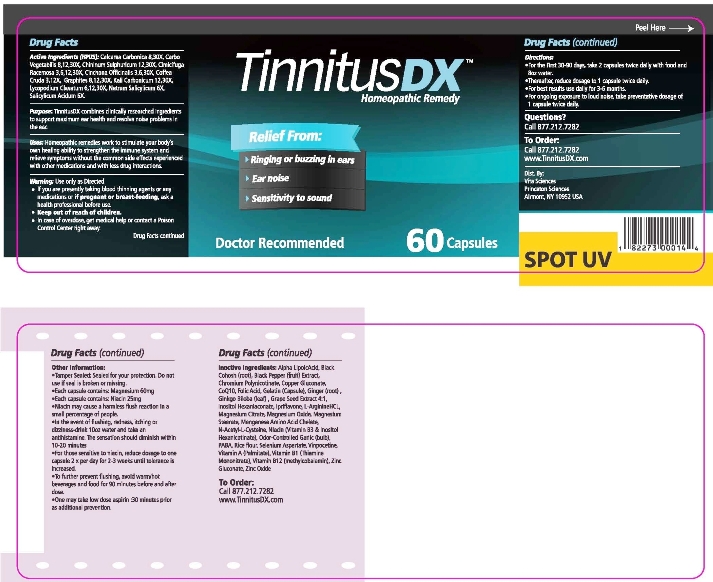 DRUG LABEL: Tinnitus
NDC: 57520-0363 | Form: CAPSULE
Manufacturer: Apotheca Company
Category: homeopathic | Type: HUMAN OTC DRUG LABEL
Date: 20110330

ACTIVE INGREDIENTS: OYSTER SHELL CALCIUM CARBONATE, CRUDE 30 [hp_X]/1 1; ACTIVATED CHARCOAL 30 [hp_X]/1 1; QUININE SULFATE 30 [hp_X]/1 1; BLACK COHOSH 30 [hp_X]/1 1; CINCHONA OFFICINALIS BARK 30 [hp_X]/1 1; ARABICA COFFEE BEAN 12 [hp_X]/1 1; GRAPHITE 30 [hp_X]/1 1; POTASSIUM CARBONATE 30 [hp_X]/1 1; LYCOPODIUM CLAVATUM SPORE 30 [hp_X]/1 1; SODIUM SALICYLATE 6 [hp_X]/1 1; SALICYLIC ACID 6 [hp_X]/1 1
INACTIVE INGREDIENTS: MAGNESIUM STEARATE; VITAMIN A PALMITATE; THIAMINE MONONITRATE; NIACIN; INOSITOL NIACINATE; FOLIC ACID; METHYLCOBALAMIN; MAGNESIUM CITRATE; MAGNESIUM OXIDE; ZINC GLUCONATE; ZINC OXIDE; SELENIUM; COPPER GLUCONATE; MANGANESE; ACETYLCYSTEINE; IPRIFLAVONE; GINKGO; GINGER; ALPHA LIPOIC ACID; GARLIC; AMINOBENZOIC ACID; BLACK COHOSH; VINPOCETINE; BLACK PEPPER; UBIDECARENONE; GELATIN; RICE; CHROMIUM; VITIS VINIFERA SEED

Tinnitus DX

ACTIVE INGREDIENT

ACTIVE INGREDIENTS: Calcarea carbonica 8X, 30X, Carbo vegetabilis 8X, 12X, 30X, Chininum sulphuricum 12X, 30X, Cimicifuga racemosa 3X, 6X, 12X, 30X, Cinchona officinalis 3X, 6X, 30X, Coffea cruda 3X, 12X, Graphites 8X, 12X, 30X, Kali carbonicum 12X, 30X, Lycopodium clavatum 6X, 12X, 30X, Natrum salicylicum 6X, Salicylicum acidum 6X.

PURPOSE

PURPOSE: Tinnitus DX combines clinically researched ingredients to support maximum ear health and resolve noise problems in the ear.

WARNINGS: Use only as directed.

If you are presently taking blood thinning agents or any medications or if pregnant or breast-feeding, ask a health professional before use.

Keep out of reach of children.

In case of overdose, get medical help or contact a Poison Control Center right away.

OTHER INFORMATION: Tamper sealed: Sealed for your protection. Do not use if seal is broken or missing.

Each capsule contains Magnesium 60mg

Each capsule contains Niacin 25mg

Niacin may cause a harmless flush reaction in a small percentage of people.

In the event of flushing, redness, itching or dizziness, drink 10 oz of water and take an antihistamine. The sensation should diminish within 10-20 minutes.

For those sensitive to niacin, reduce dosage to one capsule 2 x per day for 2-3 weeks until tolerance is increased.

To further prevent flushing, avoid warm/hot beverages and food for 90 minutes before and after dose.

One may take low dose aspirin 30 minutes prior as additional prevention.

DOSAGE AND ADMINISTRATION

DIRECTIONS: For the first 30-90 days, take 2 capsules twice daily with food and 8 oz water.

Thereafter, reduce dosage to 1 capsule twice daily.

For best results use daily for 3-5 months.

For ongoing exposure to loud noise, take preventative dosage of 1 capsule twice daily.

INACTIVE INGREDIENT

INACTIVE INGREDIENTS: Magnesium stearate, Vitamin A palmitate, Thiamine mononitrate, Vitamin B3, Niacin (from Inositol hexanicotinate), Folic acid, Vitamin B12, Magnesium citrate, Magnesium oxide, Zinc gluconate, Zinc oxide, Selenium, Copper gluconate, Manganese, Chromium, L-arginine HCL, N-acetyl-L-cysteine, Ipriflavone, Ginkgo, Grape (seed), Ginger (root), Alpha lipoic acid, Garlic (bulb), PABA (Para-aminobenzoic acid), Black cohosh, Vinpocetine, Black pepper (fruit), Cownzyme Q10, Gelatin, Rice flour.

KEEP OUT OF REACH OF CHILDREN. In case of overdose, get medical help or contact a Poison Control Center right away.

INDICATIONS AND USAGE

PURPOSE: Tinnitus DX combines clinically researched ingredients to support maximum ear health and resolve noise problems in the ear.

Questions?

Call 877-212-7282

Dist By:

Vita Sciences

Princeton Sciences

Almont, NY 10952 USA

PACKAGE LABEL

Tinnitus DX

Homeopathic Remedy

Relief from:

Ringing or buzzing in ears

Ear noise

Sensitivity to sound

Doctor Recommended

60 Capsules